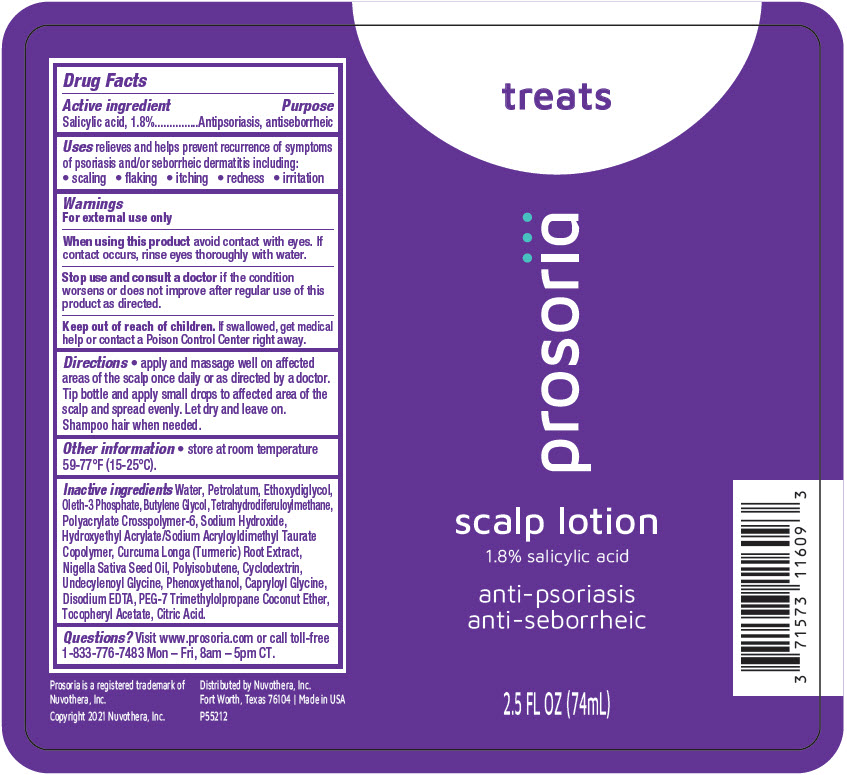 DRUG LABEL: Prosoria Scalp
NDC: 71573-116 | Form: LOTION/SHAMPOO
Manufacturer: Nuvothera, Inc.
Category: otc | Type: HUMAN OTC DRUG LABEL
Date: 20240110

ACTIVE INGREDIENTS: Salicylic Acid 1.33 g/74 mL
INACTIVE INGREDIENTS: Water; Diethylene Glycol Monoethyl Ether; AMMONIUM ACRYLOYLDIMETHYLTAURATE, DIMETHYLACRYLAMIDE, LAURYL METHACRYLATE AND LAURETH-4 METHACRYLATE COPOLYMER, TRIMETHYLOLPROPANE TRIACRYLATE CROSSLINKED (45000 MPA.S); Tetrahydrodiferuloylmethane; TURMERIC; Petrolatum; Oleth-3 Phosphate; Edetate Disodium Anhydrous; Sodium Hydroxide; Butylene Glycol; Nigella Sativa Seed Oil; Citric Acid Monohydrate; .ALPHA.-TOCOPHEROL ACETATE; POLYISOBUTYLENE (1300 MW); BETADEX; Phenoxyethanol; HYDROXYETHYL ACRYLATE/SODIUM ACRYLOYLDIMETHYL TAURATE COPOLYMER (100000 MPA.S AT 1.5%); Undecylenoyl Glycine; Capryloyl Glycine; PEG-7 Trimethylolpropane Coconut Ether

Prosoriä Scalp Lotion

Drug Facts

Active ingredient

Salicylic acid, 1.8%

Purpose

Antipsoriasis, antiseborrheic

Uses

relieves and helps prevent recurrence of symptoms of psoriasis and/or seborrheic dermatitis including:

- scaling
- flaking
- itching
- redness
- irritation

Warnings

For external use only

When using this product avoid contact with eyes. If contact occurs, rinse eyes thoroughly with water.

Stop use and consult a doctor if the condition worsens or does not improve after regular use of this product as directed.

Keep out of reach of children. If swallowed, get medical help or contact a Poison Control Center right away.

Directions

- apply and massage well on affected areas of the scalp once daily or as directed by a doctor. Tip bottle and apply small drops to affected area of the scalp and spread evenly. Let dry and leave on. Shampoo hair when needed.

Other information

- store at room temperature 59-77°F (15-25°C).

Inactive ingredients

Water, Petrolatum, Ethoxydiglycol, Oleth-3 Phosphate, Butylene Glycol, Tetrahydrodiferuloylmethane, Polyacrylate Crosspolymer-6, Sodium Hydroxide, Hydroxyethyl Acrylate/Sodium Acryloyldimethyl Taurate Copolymer, Curcuma Longa (Turmeric) Root Extract, Nigella Sativa Seed Oil, Polyisobutene, Cyclodextrin, Undecylenoyl Glycine, Phenoxyethanol, Capryloyl Glycine, Disodium EDTA, PEG-7 Trimethylolpropane Coconut Ether, Tocopheryl Acetate, Citric Acid.

Questions?

Visit www.prosoria.com or call toll-free 1-833-776-7483 Mon – Fri, 8am – 5pm CT.

Distributed by Nuvothera, Inc.
Fort Worth, Texas 76104

PRINCIPAL DISPLAY PANEL - 74 mL Bottle Label

treats

prosoriä

scalp lotion

1.8% salicylic acid

anti-psoriasis
anti-seborrheic

2.5 FL OZ (74mL)